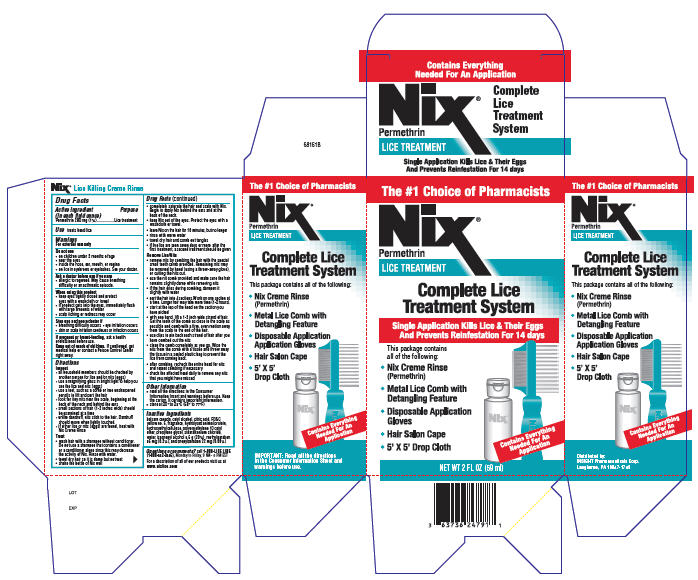 DRUG LABEL: Nix
NDC: 63736-024 | Form: SHAMPOO
Manufacturer: Insight Pharmaceuticals
Category: otc | Type: HUMAN OTC DRUG LABEL
Date: 20090610

ACTIVE INGREDIENTS: Permethrin 560 mg/59 mL
INACTIVE INGREDIENTS: Cetyl alcohol; citric acid monohydrate; FD&C yellow no. 6; propylene glycol; stearalkonium chloride; water; isopropyl alcohol; methylparaben; propylparaben

Nix® Lice Killing Creme Rinse

Drug Facts

Active ingredient
(in each fluid ounce)

Purpose

Permethrin 280 mg (1%)...................Lice treatment

Use

treats head lice

Warnings

For external use only

Do not use

- on children under 2 months of age
- near the eyes
- inside the nose, ear, mouth, or vagina
- on lice in eyebrows or eyelashes. See your doctor.

Ask a doctor before use if you are

- allergic to ragweed. May cause breathing difficulty or an asthmatic episode.

When using this product

- keep eyes tightly closed and protect eyes with a washcloth or towel
- if product gets into the eyes, immediately flush with large amounts of water
- scalp itching or redness may occur

Stop use and see a doctor if

- breathing difficulty occurs
- eye irritation occurs
- skin or scalp irritation continues or infection occurs

PREGNANCY OR BREAST FEEDING

If pregnant or breast-feeding, ask a health professional before use.

Keep out of reach of children. If swallowed, get medical help or contact a Poison Control Center right away.

Directions

Inspect

- all household members should be checked by another person for lice and/or nits (eggs)
- use a magnifying glass in bright light to help you see the lice and nits (eggs)
- use a tool, such as a comb or two unsharpened pencils to lift and part the hair
- look for tiny nits near the scalp, beginning at the back of the neck and behind the ears
- small sections of hair (1-2 inches wide) should be examined at a time
- unlike dandruff, nits stick to the hair. Dandruff should move when lightly touched.
- if either lice or nits (eggs) are found, treat with Nix Creme Rinse

Treat

- wash hair with a shampoo without conditioner. Do not use a shampoo that contains a conditioner or a conditioner alone since this may decrease the activity of Nix. Rinse with water.
- towel dry hair so it is damp but not wet
- shake the bottle of Nix well
- completely saturate the hair and scalp with Nix. Begin to apply Nix behind the ears and at the back of the neck.
- keep Nix out of the eyes. Protect the eyes with a washcloth or towel.
- leave Nix on the hair for 10 minutes, but no longer
- rinse with warm water
- towel dry hair and comb out tangles
- if live lice are seen seven days or more after the first treatment, a second treatment should be given

Remove Lice/Nits

- remove nits by combing the hair with the special small tooth comb provided. Remaining nits may be removed by hand (using a throw-away glove), or cutting the nits out.
- use the nit comb provided and make sure the hair remains slightly damp while removing nits
- if the hair dries during combing, dampen it slightly with water
- part the hair into 4 sections. Work on one section at a time. Longer hair may take more time (1-2 hours).
- start at the top of the head on the section you have picked
- with one hand, lift a 1-2 inch wide strand of hair. Get the teeth of the comb as close to the scalp as possible and comb with a firm, even motion away from the scalp to the end of the hair.
- use clips to pin back each strand of hair after you have combed out the nits
- clean the comb completely as you go. Wipe the nits from the comb with a tissue and throw away the tissue in a sealed plastic bag to prevent the lice from coming back.
- after combing, recheck the entire head for nits and repeat combing if necessary
- check the affected head daily to remove any nits that you might have missed

Other information

- read all the directions in the Consumer Information Insert and warnings before use. Keep the carton. It contains important information.
- store at 20° to 25°C (68° to 77°F)

Inactive ingredients

balsam canada, cetyl alcohol, citric acid, FD&C yellow no. 6, fragrance, hydrolyzed animal protein, hydroxyethylcellulose, polyoxyethylene 10 cetyl ether, propylene glycol, stearalkonium chloride, water, isopropyl alcohol 5.6 g (20%), methylparaben 56 mg (0.2%), and propylparaben 22 mg (0.08%)

Questions or comments?

call 1-888-LICE LINE (1-888-542-3546), Monday to Friday, 9 AM - 5 PM EST

For a description of all of our products visit us at www.nixlice.com

PRINCIPAL DISPLAY PANEL - 2 FL OZ Bottle Carton

The #1 Choice of Pharmacists

Nix®
Permethrin
LICE TREATMENT

Complete Lice
Treatment System

Single Application Kills Lice & Their Eggs
And Prevents Reinfestation For 14 days

This package contains
all of the following:

- Nix Creme Rinse
  (Permethrin)
- Metal Lice Comb with
  Detangling Feature
- Disposable Application
  Gloves
- Hair Salon Cape
- 5' × 5' Drop Cloth

Contains Everything
Needed For An
Application

NET WT 2 FL OZ (59 ml)

NIX® Creme Rinse

INDICATIONS

NIX® Creme Rinse is indicated for the treatment of infestation with head lice and their nits (eggs). This unique creme rinse leaves the hair manageable and easy to comb.

WHAT ARE HEAD LICE?

Head lice are small insects that live and feed on the human scalp causing itching and irritation. They range in colour from beige to black. Lice lay eggs, called nits, on the hair shaft close to the scalp. The nits are tiny, oval shaped and shiny, and range in colour from creamy white to brown. Nits normally hatch in 7 to 10 days. The adult lice cannot survive away from the head for much more than 24 hours.

HOW DOES A LICE INFESTATION SPREAD?

Head lice spread easily, primarily by close head-to-head contact with persons who have lice and occasionally by sharing personal articles such as clothing, hats, combs, hair accessories, towels and bed linen.

WHAT TO DO IF YOU OR A MEMBER OF YOUR FAMILY HAS HEAD LICE

Head lice affect millions of people each year, especially school-aged children. They do not transmit or cause disease and are not a sign of poor personal hygiene. A head lice infestation can be effectively treated with a topical pediculicide and ovicide treatment (a treatment effective at destroying lice and their eggs) such as NIX Creme Rinse.

DIRECTIONS FOR USE OF NIX® CREME RINSE

1. Wash the hair with conditioner-free shampoo. Do not use a conditioner. Rinse with water and towel dry thoroughly.
2. Shake NIX bottle well. Apply a sufficient amount of NIX (1/2 to 1 bottle) to thoroughly saturate the hair and scalp, especially behind the ears and at the base of the neck.
3. Leave NIX on the hair for 10 minutes.
4. Rinse NIX off hair with water.
5. Towel dry hair.
6. Comb hair with regular comb to remove tangles.
7. Remove nits: Part hair into sections; starting as close to the scalp as possible, remove the nits using the nit removal comb provided. Be sure to comb to the end of the hair shaft. The nit comb should be disinfected by soaking in hot water after each use. Inspect full head of hair thoroughly for any stray nits. The nit removal procedure should be repeated daily for the 7 days following treatment.

A single application is usually sufficient to eliminate a head lice infestation. The active ingredient in NIX persists on the hair for 10 days, even after subsequent washing with a conditioner-free shampoo. If you see live lice or nits after the first application, the residual effect should kill these. If you still see live lice or nits on the 7th day (or after) following the first application, NIX Creme Rinse should be applied a second time, as described above.

HOW TO HELP PREVENT REINFESTATION

Cleaning of personal articles is also an important part of head lice management and may help prevent reinfestation. Personal belongings including recently worn clothing, towels and bed linens should be machine washed in hot water and dried using the hot cycle of the dryer for at least 20 minutes. Personal articles of clothing or bedding that cannot be washed may be dry cleaned or sealed in a plastic bag for a period of two weeks. Combs and brushes should be disinfected by soaking in hot water (above 130°F/54°C) for 5 to 10 minutes.

Children should be advised not to use any borrowed combs or brushes, nor wear anyone else's clothes, especially hats.

Inspect all family members from time to time for any new lice infestation. If a new infestation is found treat with NIX Creme Rinse.

PRECAUTIONS

General: Head lice infestation is often accompanied by itching, redness, and swelling. Treatment with NIX may temporarily worsen these conditions. Do not use if allergic to any of its ingredients, synthetic pyrethroids or pyrethrin, or chrysanthemums. Discontinue use if reaction occurs.

Eye Irritation: NIX is not irritating to eyes; however, if it should get into them, rinse eyes immediately with water.

In Case of Swallowing: Consult your doctor or Poison Control Centre immediately.

Use in Pregnant or Nursing Women: There are no adequate or well-controlled studies in pregnant or nursing women. Consult a doctor before using this drug.

Use in Children: NIX is safe and effective in children two months of age and older. Safety and effectiveness in children less than two months of age have not been established. Consult your doctor.

Keep out of reach of children. To prevent accidental ingestion by children, the remaining contents of NIX should be discarded after use.

ADVERSE REACTIONS

In clinical studies, occasional itching has been known to occur. This is usually a consequence of head lice infestation itself, but may be temporarily worsened following treatment with NIX. Other reactions which are less frequent include: stinging/burning, tingling, numbness or discomfort, redness, and swelling or rash of the scalp. All these reactions are mild and temporary.

MEDICINAL INGREDIENT

Permethrin is the active ingredient in NIX Creme Rinse; it is present at a concentration of 1%.

NON-MEDICINAL INGREDIENTS (ALPHABETICALLY)

In addition, NIX Creme Rinse also contains the following non-active components: balsam Canada, cetyl alcohol, citric acid, FD&C Yellow No. 6, fragrance, hydrolyzed animal protein, hydroxyethylcellulose, isopropyl alcohol, parabens, polyoxyethylene cetyl ether, propylene glycol, stearalkonium chloride and water.

Comments or Questions ? 1-888-542-3546 or visit us at www.insightpharma.com
Distributed by: INSIGHT Pharmaceuticals Corp.
Langhorne, PA 19049-1749

66621A